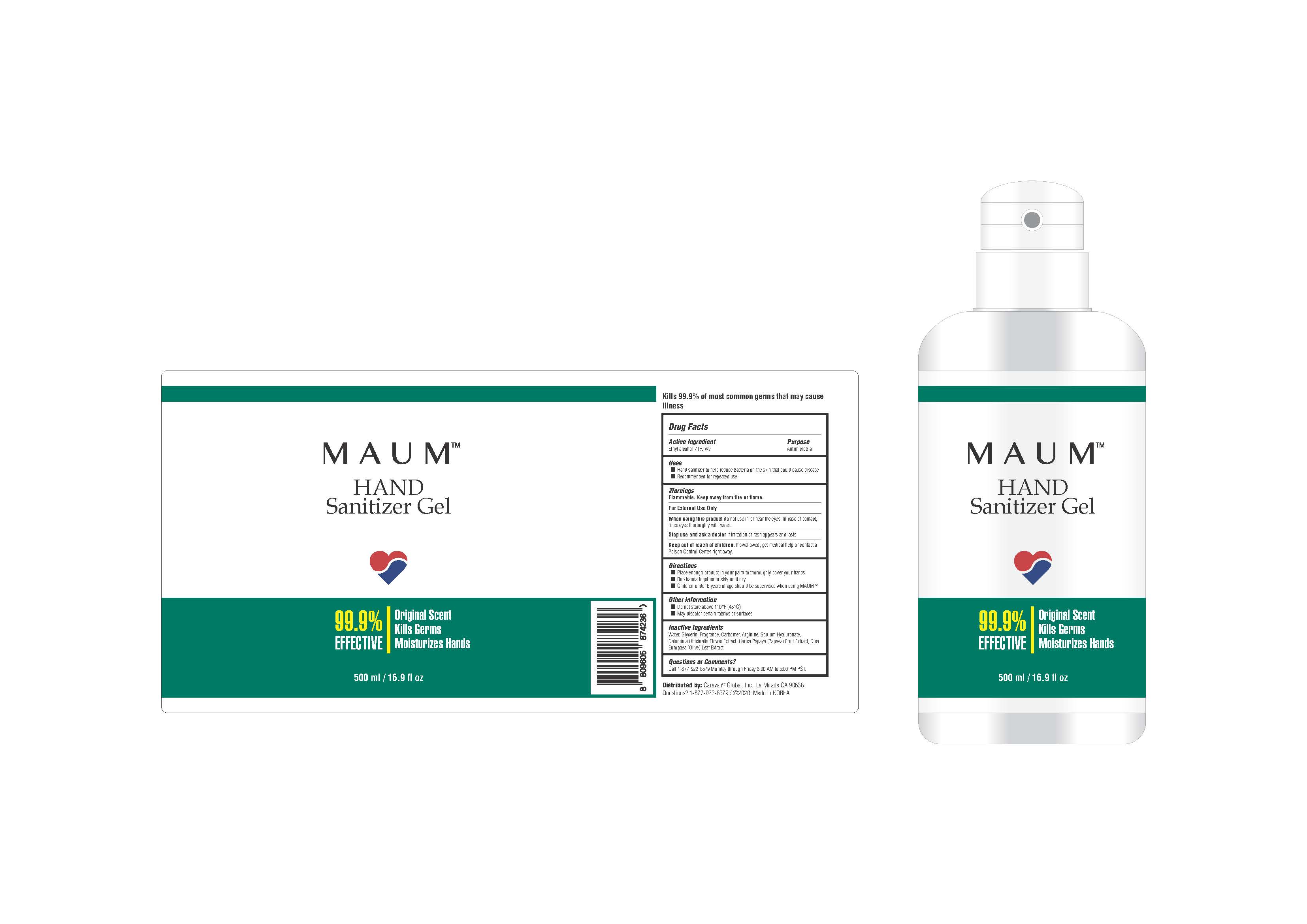 DRUG LABEL: MAUM Hand Sanitizer gel
NDC: 71909-0002 | Form: GEL
Manufacturer: Cnt Dream. Co., Ltd
Category: otc | Type: HUMAN OTC DRUG LABEL
Date: 20200413

ACTIVE INGREDIENTS: ALCOHOL 355 mL/500 mL
INACTIVE INGREDIENTS: WATER

CNT DREAM (AMARTE) - MAUM Hand Sanitizer gel

ACTIVE INGREDIENT

Alcohol

INACTIVE INGREDIENT

water, etc

PURPOSE

Antiseptic

keep out of reach of the children

INDICATIONS AND USAGE

Place enough product in your palm to thoroughly spread on both hands and rub into the skin until dry.

Supervise children in the use of this product.

WARNINGS

For external use only.

Flammable.

Keep away from fire or flame.

DOSAGE AND ADMINISTRATION

for external use only